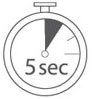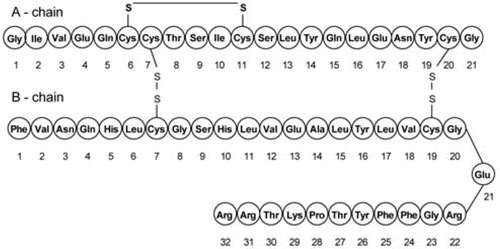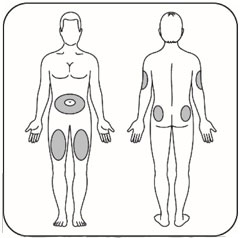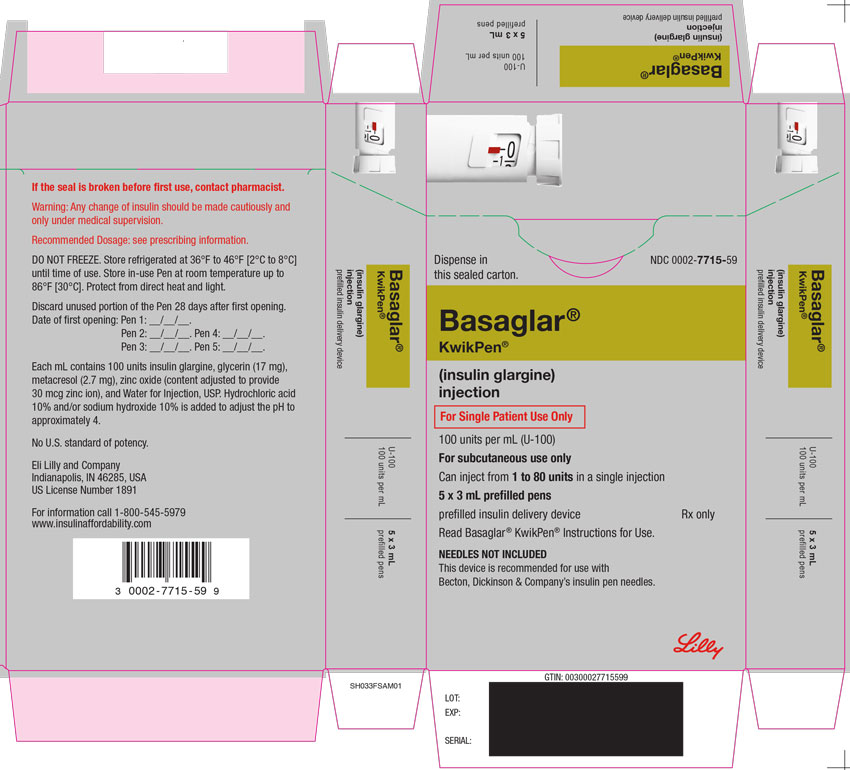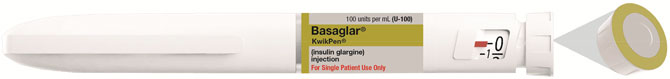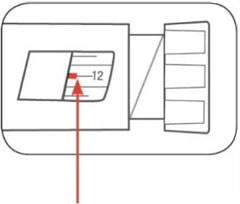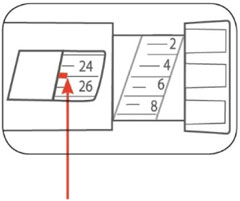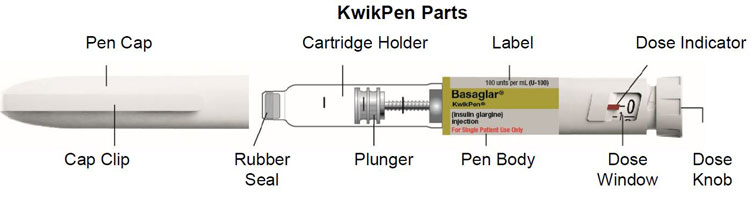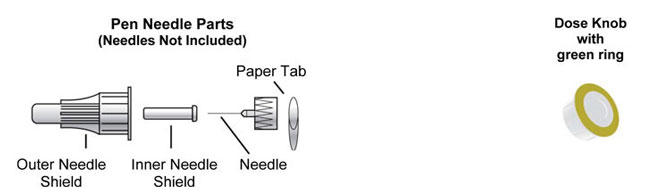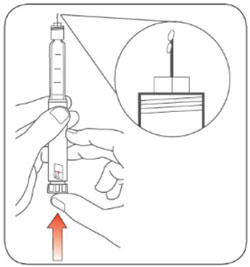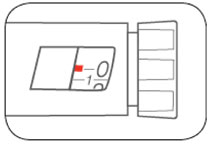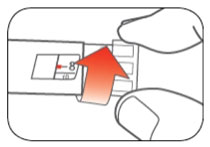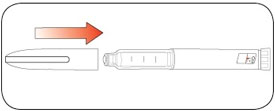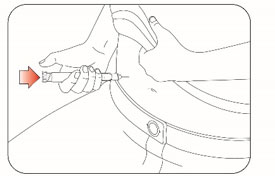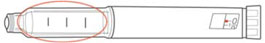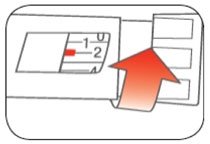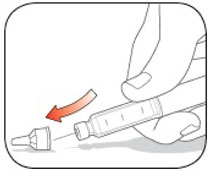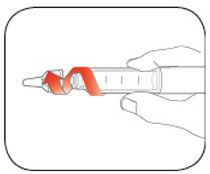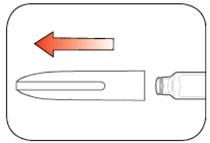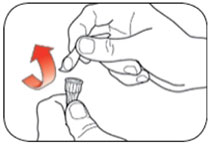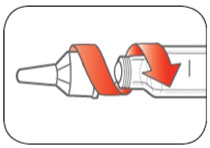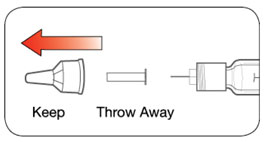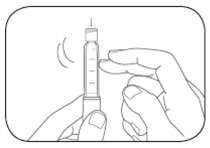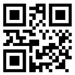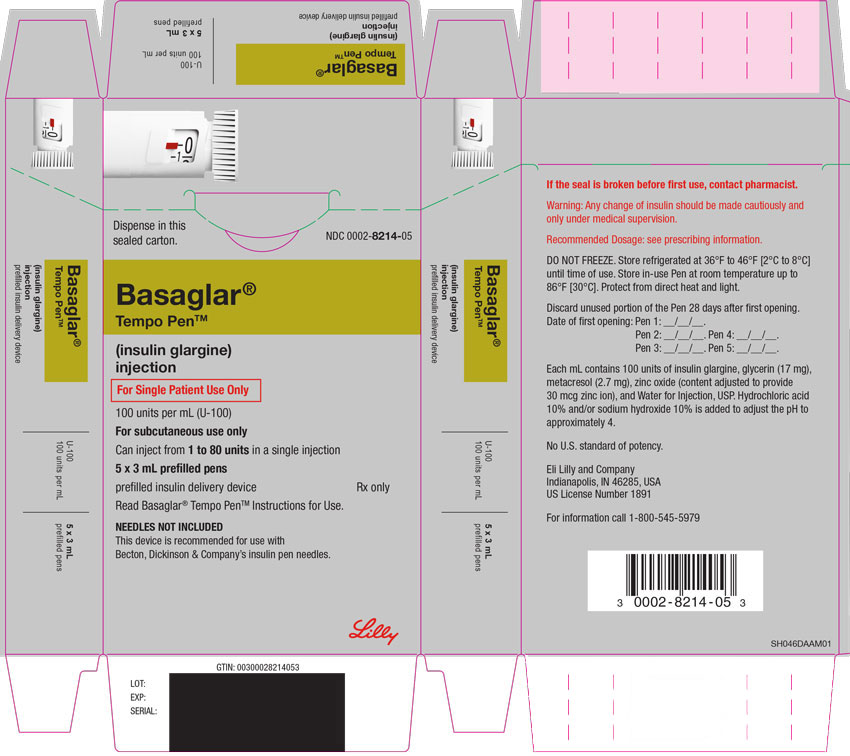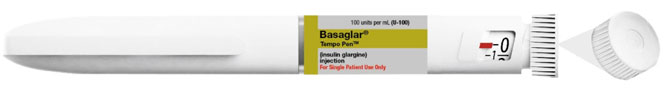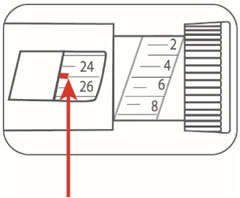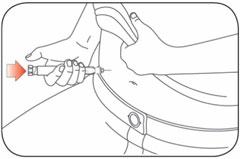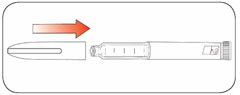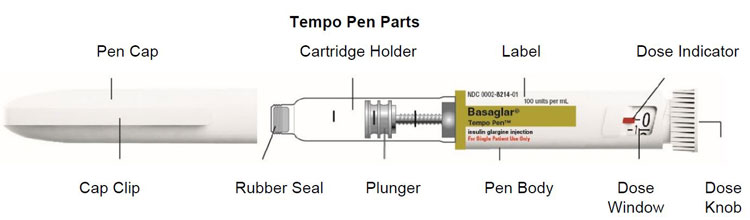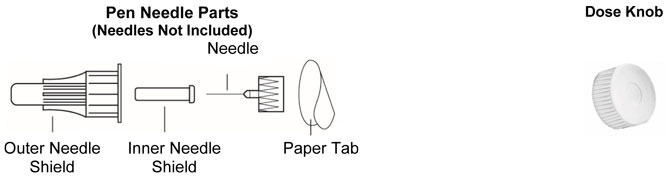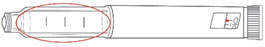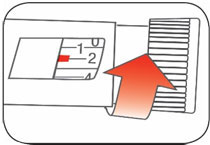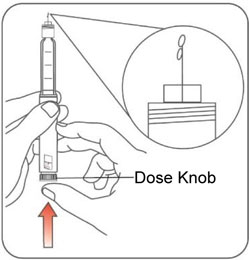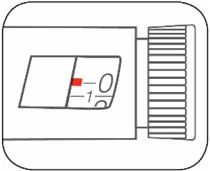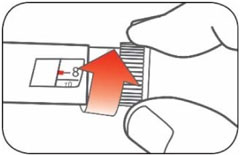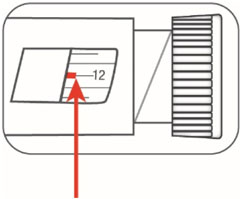 DRUG LABEL: BASAGLAR 
NDC: 0002-7715 | Form: INJECTION, SOLUTION
Manufacturer: Eli Lilly and Company
Category: prescription | Type: HUMAN PRESCRIPTION DRUG LABEL
Date: 20251211

ACTIVE INGREDIENTS: Insulin glargine 100 [iU]/1 mL
INACTIVE INGREDIENTS: Glycerin 17 mg/1 mL; Metacresol 2.7 mg/1 mL; Zinc oxide 0.03 mg/1 mL; Hydrochloric acid; Sodium hydroxide; Water

HIGHLIGHTS OF PRESCRIBING INFORMATION

These highlights do not include all the information needed to use BASAGLAR safely and effectively. See full prescribing information for BASAGLAR
BASAGLAR (insulin glargine) injection, for subcutaneous use
Initial U.S. Approval: 2015

1 INDICATIONS AND USAGE

BASAGLAR® is a long-acting human insulin analog indicated to improve glycemic control in adults and pediatric patients with type 1 diabetes mellitus and in adults with type 2 diabetes mellitus. (1)

Limitations of Use:
Not recommended for treating diabetic ketoacidosis. (1)

2 DOSAGE AND ADMINISTRATION

- Individualize dosage based on metabolic needs, blood glucose monitoring, glycemic control, type of diabetes, prior insulin use. (2.2, 2.3, 2.4)
- Administer subcutaneously once daily at any time of day, but at the same time every day. (2.2)
- Rotate injection sites into the abdominal area, thigh, or deltoid to reduce the risk of lipodystrophy and localized cutaneous amyloidosis. (2.1)
- Closely monitor glucose when converting to BASAGLAR and during initial weeks thereafter. (2.2)
- Do not dilute or mix with any other insulin or solution. (2.1)

3 DOSAGE FORMS AND STRENGTHS

Injection: 100 units/mL (U-100) is available as: (3)

- 3 mL single-patient-use BASAGLAR KwikPen®
- 3 mL single-patient-use BASAGLAR Tempo PenTM

4 CONTRAINDICATIONS

- During episodes of hypoglycemia. (4)
- Hypersensitivity to BASAGLAR or any of its excipients. (4)

5 WARNINGS AND PRECAUTIONS

- Never share a BASAGLAR prefilled pen between patients, even if the needle is changed. (5.1)
- Hyperglycemia or hypoglycemia with changes in insulin regimen: Make changes to a patient's insulin regimen (e.g., insulin strength, manufacturer, type, injection site or method of administration) under close medical supervision with increased frequency of blood glucose monitoring. (5.2)
- Hypoglycemia: May be life-threatening. Increase frequency of glucose monitoring with changes to: insulin dosage, co-administered glucose lowering medications, meal pattern, physical activity; and in patients with renal or hepatic impairment and hypoglycemia unawareness. (5.3, 6.1)
- Hypoglycemia due to medication errors: Accidental mix-ups between insulin products can occur. Instruct patients to check insulin labels before injection. (5.4)
- Hypersensitivity reactions: Severe, life-threatening, generalized allergy, including anaphylaxis, can occur. Discontinue BASAGLAR, monitor and treat if indicated. (5.5, 6.1)
- Hypokalemia: May be life-threatening. Monitor potassium levels in patients at risk of hypokalemia and treat if indicated. (5.6)
- Fluid retention and heart failure with concomitant use of thiazolidinediones (TZDs): Observe for signs and symptoms of heart failure; consider dosage reduction or discontinuation if heart failure occurs. (5.7)

6 ADVERSE REACTIONS

Adverse reactions commonly (≥5%) associated with insulin glargine products are: Hypoglycemia, allergic reactions, injection site reaction, lipodystrophy, pruritus, rash, edema, and weight gain. (6.1)

To report SUSPECTED ADVERSE REACTIONS, contact Eli Lilly and Company at 1-800-LillyRx (1-800-545-5979) or FDA at 1-800-FDA-1088 or www.fda.gov/medwatch.

7 DRUG INTERACTIONS

- Drugs that may increase the risk of hypoglycemia: antidiabetic agents, ACE inhibitors, angiotensin II receptor blocking agents, disopyramide, fibrates, fluoxetine, monoamine oxidase inhibitors, pentoxifylline, pramlintide, salicylates, somatostatin analog (e.g., octreotide), and sulfonamide antibiotics (7).
- Drugs that may decrease the blood glucose lowering effect: atypical antipsychotics, corticosteroids, danazol, diuretics, estrogens, glucagon, isoniazid, niacin, oral contraceptives, phenothiazines, progestogens (e.g., in oral contraceptives), protease inhibitors, somatropin, sympathomimetic agents (e.g., albuterol, epinephrine, terbutaline), and thyroid hormones (7).
- Drugs that may increase or decrease the blood glucose lowering effect: alcohol, beta-blockers, clonidine, lithium salts, and pentamidine (7).
- Drugs that may blunt the signs and symptoms of hypoglycemia: beta-blockers, clonidine, guanethidine, and reserpine (7).

FULL PRESCRIBING INFORMATION

1 INDICATIONS AND USAGE

BASAGLAR® is indicated to improve glycemic control in adults and pediatric patients with type 1 diabetes mellitus and in adults with type 2 diabetes mellitus.

Limitations of Use

BASAGLAR is not recommended for the treatment of diabetic ketoacidosis.

2 DOSAGE AND ADMINISTRATION

2.1 Important Administration Instructions

- Always check insulin labels before administration [see Warnings and Precautions (5.4)].
- Visually inspect BASAGLAR prefilled pens for particulate matter and discoloration prior to administration. Only use if the solution is clear and colorless with no visible particles.
- Administer BASAGLAR subcutaneously into the abdominal area, thigh, or deltoid, and rotate injection sites within the same region from one injection to the next to reduce the risk of lipodystrophy and localized cutaneous amyloidosis. Do not inject into areas of lipodystrophy or localized cutaneous amyloidosis [see Warnings and Precautions (5.2) and Adverse Reactions (6)].
- During changes to a patient's insulin regimen, increase the frequency of blood glucose monitoring [see Warnings and Precautions (5.2)].
- Use BASAGLAR with caution in patients with visual impairment that may rely on audible clicks to dial their dose.
- Do not dilute or mix BASAGLAR with any other insulin or solution.
- Do not administer intravenously or via an insulin pump.

2.2 General Dosing Instructions

- In patients with type 1 diabetes, BASAGLAR must be used concomitantly with short-acting insulin.
- Inject BASAGLAR subcutaneously once daily at any time of day but at the same time every day.
- Individualize and adjust the dosage of BASAGLAR based on the individual's metabolic needs, blood glucose monitoring results and glycemic control goal.
- Dosage adjustments may be needed with changes in physical activity, changes in meal patterns (i.e., macronutrient content or timing of food intake), during acute illness, or changes in renal or hepatic function. Dosage adjustments should only be made under medical supervision with appropriate glucose monitoring [see Warnings and Precautions (5.2)].
- The BASAGLAR prefilled pens each dials in 1 unit increments and delivers a maximum dose of 80 units per injection.

2.3 Initiation of BASAGLAR Therapy

- The recommended starting dose of BASAGLAR in patients with type 1 diabetes should be approximately one-third of the total daily insulin requirements. Short- or rapid-acting, pre-meal insulin should be used to satisfy the remainder of the daily insulin requirements.
- The recommended starting dose of BASAGLAR in patients with type 2 diabetes is 0.2 units/kg or up to 10 units once daily.

2.4 Changing to BASAGLAR from Other Insulin Therapies

- If changing patients from another insulin glargine product, 100 units/mL, to BASAGLAR, the dose of BASAGLAR should be the same as the other insulin glargine product, 100 units/mL.
- If changing patients from a once-daily insulin glargine product, 300 units/mL, to once-daily BASAGLAR, the recommended initial BASAGLAR dosage is 80% of the insulin glargine product, 300 units/mL [see Warnings and Precautions (5.2)].
- If changing from a treatment regimen with an intermediate- or long-acting insulin to a regimen with BASAGLAR, a change in the dose of the basal insulin may be required.
- If changing patients from twice-daily NPH insulin to once-daily BASAGLAR, the recommended initial BASAGLAR dosage is 80% of the total daily NPH dosage [see Warnings and Precautions (5.2)].

3 DOSAGE FORMS AND STRENGTHS

Injection: 100 units/mL (U-100) clear and colorless solution available as:

- 3 mL single-patient-use BASAGLAR KwikPen
- 3 mL single-patient-use BASAGLAR Tempo Pen

4 CONTRAINDICATIONS

BASAGLAR is contraindicated:

- During episodes of hypoglycemia [see Warnings and Precautions (5.3)].
- In patients with hypersensitivity to insulin glargine or any of the excipients in BASAGLAR [see Warnings and Precautions (5.5)].

5 WARNINGS AND PRECAUTIONS

5.1 Never Share a BASAGLAR Prefilled Pen Between Patients

BASAGLAR prefilled pens must never be shared between patients, even if the needle is changed. Sharing poses a risk for transmission of blood-borne pathogens.

5.2 Hyperglycemia or Hypoglycemia with Changes in Insulin Regimen

Changes in an insulin regimen (e.g., insulin strength, manufacturer, type, injection site or method of administration) may affect glycemic control and predispose to hypoglycemia [see Warnings and Precautions (5.3)] or hyperglycemia. Repeated insulin injections into areas of lipodystrophy or localized cutaneous amyloidosis have been reported to result in hyperglycemia; and a sudden change in the injection site (to an unaffected area) has been reported to result in hypoglycemia [see Adverse Reactions (6)].

Make any changes to a patient's insulin regimen under close medical supervision with increased frequency of blood glucose monitoring. Advise patients who have repeatedly injected into areas of lipodystrophy or localized cutaneous amyloidosis to change the injection site to unaffected areas and closely monitor for hypoglycemia. For patients with type 2 diabetes, dosage adjustments of concomitant anti-diabetic products may be needed.

5.3 Hypoglycemia

Hypoglycemia is the most common adverse reaction associated with insulins, including BASAGLAR [see Adverse Reactions (6.1)]. Severe hypoglycemia can cause seizures, may be life-threatening or cause death. Hypoglycemia can impair concentration ability and reaction time; this may place an individual and others at risk in situations where these abilities are important (e.g., driving or operating other machinery). BASAGLAR, or any insulin, should not be used during episodes of hypoglycemia [see Contraindications (4)].

Hypoglycemia can happen suddenly and symptoms may differ in each individual and change over time in the same individual. Symptomatic awareness of hypoglycemia may be less pronounced in patients with longstanding diabetes, in patients with diabetic nerve disease, in patients using medications that block the sympathetic nervous system (e.g., beta-blockers) [see Drug Interactions (7)], or in patients who experience recurrent hypoglycemia.

Risk Factors for Hypoglycemia

The risk of hypoglycemia after an injection is related to the duration of action of the insulin and, in general, is highest when the glucose lowering effect of the insulin is maximal. As with all insulins, the glucose lowering effect time course of BASAGLAR may vary in different individuals or at different times in the same individual and depends on many conditions, including the area of injection as well as the injection site blood supply and temperature [see Clinical Pharmacology (12.2)]. The risk of hypoglycemia generally increases with intensity of glycemic control. Other factors which may increase the risk of hypoglycemia include changes in meal pattern (e.g., macronutrient content or timing of meals), changes in level of physical activity, or changes to co-administered medication [see Drug Interactions (7)]. Patients with renal or hepatic impairment may be at higher risk of hypoglycemia [see Use in Specific Populations (8.6, 8.7)].

Risk Mitigation Strategies for Hypoglycemia

Patients and caregivers must be educated to recognize and manage hypoglycemia. Self-monitoring of blood glucose plays an essential role in the prevention and management of hypoglycemia. In patients at higher risk for hypoglycemia and patients who have reduced symptomatic awareness of hypoglycemia, increased frequency of blood glucose monitoring is recommended.

The long-acting effect of BASAGLAR may delay recovery from hypoglycemia.

5.4 Hypoglycemia Due to Medication Errors

Accidental mix-ups between insulin products have been reported. To avoid medication errors between BASAGLAR and other insulins, instruct patients to always check the insulin label before each injection.

5.5 Hypersensitivity Reactions

Severe, life-threatening, generalized allergy, including anaphylaxis, can occur with insulins, including BASAGLAR. If hypersensitivity reactions occur, discontinue BASAGLAR; treat per standard of care and monitor until symptoms and signs resolve [see Adverse Reactions (6.1)]. BASAGLAR is contraindicated in patients who have had hypersensitivity reactions to insulin glargine or one of the excipients [see Contraindications (4)].

5.6 Hypokalemia

All insulins, including BASAGLAR, cause a shift in potassium from the extracellular to intracellular space, possibly leading to hypokalemia. Untreated hypokalemia may cause respiratory paralysis, ventricular arrhythmia, and death. Monitor potassium levels in patients at risk for hypokalemia if indicated (e.g., patients using potassium-lowering medications, patients taking medications sensitive to serum potassium concentrations).

5.7 Fluid Retention and Heart Failure with Concomitant Use of PPAR-gamma Agonists

Thiazolidinediones (TZDs), which are peroxisome proliferator-activated receptor (PPAR)-gamma agonists, can cause dose-related fluid retention, particularly when used in combination with insulin. Fluid retention may lead to or exacerbate heart failure. Patients treated with insulin, including BASAGLAR, and a PPAR-gamma agonist should be observed for signs and symptoms of heart failure. If heart failure develops, it should be managed according to current standards of care, and discontinuation or dose reduction of the PPAR-gamma agonist must be considered.

6 ADVERSE REACTIONS

The following adverse reactions are discussed elsewhere:

- Hypoglycemia [see Warnings and Precautions (5.3)].
- Hypoglycemia Due to Medication Errors [see Warnings and Precautions (5.4)].
- Hypersensitivity Reactions [see Warnings and Precautions (5.5)].
- Hypokalemia [see Warnings and Precautions (5.6)].

6.1 Clinical Trial Experience

Because clinical trials are conducted under widely varying conditions, adverse reaction rates observed in the clinical trials of a drug cannot be directly compared to rates in the clinical trials of another drug and may not reflect the rates observed in practice.

Two clinical trials with BASAGLAR were conducted: one in type 1 diabetes and one in type 2 diabetes.

The type 1 diabetes population had the following characteristics: Mean age was 41 years and mean duration of diabetes was 16 years. 58% were male. 75% were Caucasian, 2% Black or African American and 4% American Indian or Alaskan native. 4% were Hispanic. At baseline, mean eGFR was 109 mL/min/1.73m^2. 73.5 percent of patients had eGFR>90 mL/min/1.73m^2. The mean BMI was approximately 26 kg/m^2. HbA1c at baseline was 7.8%. The data in Table 1 reflect exposure of 268 patients to BASAGLAR with a mean exposure duration of 49 weeks.

The type 2 diabetes population had the following characteristics: Mean age was 59 years and mean duration of diabetes was 11 years. 50% were male. 78% were Caucasian, 8% Black or African American and 5% American Indian or Alaskan native. 28% were Hispanic. At baseline, mean eGFR was 109 mL/min/1.73m^2. 67.5 percent of patients had eGFR>90 mL/min/1.73m^2. The mean BMI was approximately 32 kg/m^2. HbA1c at baseline was 8.3%. The data in Table 2 reflect exposure of 376 patients to BASAGLAR with a mean exposure duration of 22 weeks.

Common adverse reactions were defined as reactions occurring in ≥5% of the population studied. Common adverse reactions during clinical trials in patients with type 1 diabetes mellitus and type 2 diabetes mellitus (other than hypoglycemia) are listed in Table 1 and Table 2, respectively.

Table 1: Adverse reactions occurring in ≥5% of adult patients with type 1 diabetes treated with BASAGLAR in a 52-week trial
 | BASAGLAR + Insulin Lispro, % (n=268)
Infectiona | 24
Nasopharyngitis | 16
Upper respiratory tract infection | 8
a Infections other than nasopharyngitis or upper respiratory tract infection.

Table 2: Adverse reactions occurring in ≥5% of adult patients with type 2 diabetes treated with BASAGLAR in a 24-week trial
 | BASAGLAR + Oral Antidiabetic Medication, % (n=376)
Infectiona | 17
Nasopharyngitis | 6
Upper respiratory tract infection | 5
a Infections other than nasopharyngitis or upper respiratory tract infection.

The frequencies of adverse reactions during a clinical trial of 5 years duration with another insulin glargine product, 100 units/mL, in patients with type 2 diabetes mellitus are listed in Table 3.

Table 3: Common adverse reactions in 5-year trial of adult patients with type 2 diabetes (adverse reactions with incidence ≥10% and higher with another insulin glargine product, 100 units/mL, than comparator)
 | Another Insulin Glargine Product, % (n=514) | NPH, % (n=503)
Hypertension | 20 | 19
Sinusitis | 19 | 18
Cataract | 18 | 16
Bronchitis | 15 | 14
Back pain | 13 | 12
Cough | 12 | 7
Urinary tract infection | 11 | 10
Diarrhea | 11 | 10
Depression | 11 | 10
Headache | 10 | 9

The frequencies of adverse reactions during clinical trials with another insulin glargine product, 100 units/mL, in children and adolescents with type 1 diabetes mellitus are listed in Table 4.

Table 4: Adverse reactions in a 28-week clinical trial of pediatric patients with type 1 diabetes (adverse reactions with frequency ≥5% and the same or higher with another insulin glargine product, 100 units/mL, than comparator)
 | Another Insulin Glargine Product, % (n=174) | NPH, % (n=175)
Rhinitis | 5 | 5

Severe Hypoglycemia

Hypoglycemia is the most commonly observed adverse reaction in patients using insulin, including BASAGLAR. The rates of reported hypoglycemia depend on the definition of hypoglycemia used, diabetes type, insulin dose, intensity of glucose control, background therapies, and other intrinsic and extrinsic patient factors. For these reasons, comparing rates of hypoglycemia in clinical trials for BASAGLAR with the incidence of hypoglycemia for other products may be misleading and also, may not be representative of hypoglycemia rates that will occur in clinical practice.

Severe symptomatic hypoglycemia was defined as an event with symptoms consistent with hypoglycemia requiring the assistance of another person and associated with either a blood glucose below 50 mg/dL (≤56 mg/dL in the 5-year trial and ≤36 mg/dL in the ORIGIN trial) or prompt recovery after oral carbohydrate, intravenous glucose or glucagon administration.

The incidence of severe symptomatic hypoglycemia in patients receiving BASAGLAR with type 1 diabetes mellitus and type 2 diabetes mellitus [see Clinical Studies (14)] was 4% at 52 weeks and 1% at 24 weeks, respectively.

The incidence of severe symptomatic hypoglycemia in a clinical trial with another insulin glargine product, 100 units/mL, in children and adolescents age 6 to 15 years with type 1 diabetes [see Clinical Studies (14)] was 23% at 26 weeks.

Table 5 displays the proportion of patients experiencing severe symptomatic hypoglycemia in another insulin glargine product, 100 units/mL, and Standard Care groups in the ORIGIN Trial [see Clinical Studies (14)].

Table 5: Severe Symptomatic Hypoglycemia in the ORIGIN Trial
 | ORIGIN Trial Median duration of follow-up: 6.2 years
 | Another Insulin Glargine Product, 100 units/mL (N=6231) | Standard Care (N=6273)
Percent of patients | 6 | 2

Allergic Reactions

Some patients taking insulins, including BASAGLAR have experienced erythema, local edema, and pruritus at the site of injection. These conditions were usually self-limiting. Severe cases of generalized allergy (anaphylaxis) have been reported.

Peripheral Edema

Some patients taking BASAGLAR have experienced sodium retention and edema, particularly if previously poor metabolic control is improved by intensified insulin therapy.

Lipodystrophy

Administration of insulins subcutaneously, including BASAGLAR, has resulted in lipoatrophy (depression in the skin) or lipohypertrophy (enlargement or thickening of tissue) in some patients [see Dosage and Administration (2.1)].

Weight gain

Weight gain has occurred with insulins, including BASAGLAR, and has been attributed to the anabolic effects of insulin and the decrease in glycosuria.

6.2 Immunogenicity

As with all therapeutic proteins, there is potential for immunogenicity.

In a 52-week study of type 1 diabetes patients, 42% of patients who received BASAGLAR once daily were positive for anti-drug antibodies (ADA) at least once during the study, including 17% that were positive at baseline and 25% of patients who developed ADA during the study. Sixty-five percent of the ADA positive patients on BASAGLAR with antibody testing at week 52 remained ADA positive at week 52.

In a 24-week study of type 2 diabetes patients, 17% of patients who received BASAGLAR once daily were positive for ADA at least once during the study. Among the subjects who were positive, 5% had ADA at baseline and 12% developed antibodies during the study. The percent binding of patients positive at baseline on BASAGLAR did not increase significantly during the study. Fifty-one percent of the ADA positive patients on BASAGLAR with antibody testing at week 24 remained ADA positive at week 24. There was no evidence that these antibodies had an impact on efficacy and safety outcomes.

The detection of antibody formation is highly dependent on the sensitivity and specificity of the assay and may be influenced by several factors such as: assay methodology, sample handling, timing of sample collection, concomitant medication, and underlying disease. For these reasons, comparison of the incidence of antibodies to BASAGLAR with the incidence of antibodies in other studies or to other products may be misleading.

6.3 Postmarketing Experience

The following adverse reactions have been identified during post-approval use of insulin glargine. Because these reactions are reported voluntarily from a population of uncertain size, it is not always possible to estimate reliably their frequency or establish a causal relationship to drug exposure.

Medication errors have been reported in which other insulin products, particularly rapid-acting insulins, have been accidentally administered instead of insulin glargine.

Localized cutaneous amyloidosis at the injection site has occurred. Hyperglycemia has been reported with repeated insulin injections into areas of localized cutaneous amyloidosis; hypoglycemia has been reported with a sudden change to an unaffected injection site.

7 DRUG INTERACTIONS

Table 6 includes clinically significant drug interactions with BASAGLAR

Table 6: Clinically Significant Drug Interactions with BASAGLAR
Drugs That May Increase the Risk of Hypoglycemia
Drugs: | Antidiabetic agents, ACE inhibitors, angiotensin II receptor blocking agents, disopyramide, fibrates, fluoxetine, monoamine oxidase inhibitors, pentoxifylline, pramlintide, salicylates, somatostatin analogs (e.g., octreotide), and sulfonamide antibiotics.
Intervention: | Dose reductions and increased frequency of glucose monitoring may be required when BASAGLAR is co-administered with these drugs.
Drugs That May Decrease the Blood Glucose Lowering Effect of BASAGLAR
Drugs: | Atypical antipsychotics (e.g., olanzapine and clozapine), corticosteroids, danazol, diuretics, estrogens, glucagon, isoniazid, niacin, oral contraceptives, phenothiazines, progestogens (e.g., in oral contraceptives), protease inhibitors, somatropin, sympathomimetic agents (e.g., albuterol, epinephrine, terbutaline), and thyroid hormones
Intervention: | Dose increases and increased frequency of glucose monitoring may be required when BASAGLAR is co-administered with these drugs.
Drugs That May Increase or Decrease the Blood Glucose Lowering Effect of BASAGLAR
Drugs: | Alcohol, beta-blockers, clonidine, and lithium salts. Pentamidine may cause hypoglycemia, which may sometimes be followed by hyperglycemia.
Intervention: | Dose adjustment and increased frequency of glucose monitoring may be required when BASAGLAR is co-administered with these drugs.
Drugs That May Blunt Signs and Symptoms of Hypoglycemia
Drugs: | beta-blockers, clonidine, guanethidine, and reserpine
Intervention: | Increased frequency of glucose monitoring may be required when BASAGLAR is co-administered with these drugs.

8 USE IN SPECIFIC POPULATIONS

8.1 Pregnancy

Risk Summary

Published studies with use of insulin glargine products during pregnancy have not reported a clear

association with insulin glargine products and adverse developmental outcomes (see Data). There are risks to the mother and fetus associated with poorly controlled diabetes in pregnancy (see Clinical Considerations). In animal reproduction studies, another insulin glargine product was administered to rats before, during and throughout pregnancy at doses up to 7 times the clinical dose of 10 units/day and to rabbits during organogenesis at doses approximately 2 times the clinical dose of 10 units/day. The effects of this other insulin glargine product did not generally differ from those observed with regular human insulin in rats or rabbits (see Data).

The estimated background risk of major birth defects is 6-10% in women with pre-gestational diabetes with a HbA1c >7 and has been reported to be as high as 20-25% in women with a HbA1c >10. The estimated background risk of miscarriage for the indicated population is unknown. In the US general population, the estimated background risk of major birth defects and miscarriage in clinically recognized pregnancies is 2-4% and 15-20%, respectively.

Clinical Considerations

Disease-associated maternal and/or embryo/fetal risk

Poorly controlled diabetes in pregnancy increases the maternal risk for diabetic ketoacidosis, pre-eclampsia, spontaneous abortions, preterm delivery, and delivery complications. Poorly controlled diabetes increases the fetal risk for major birth defects, stillbirth, and macrosomia related morbidity.

Data

Human Data

Published data do not report a clear association with insulin glargine products and major birth defects, miscarriage, or adverse maternal or fetal outcomes when insulin glargine products are used during pregnancy. However, these studies cannot definitely establish the absence of any risk because of methodological limitations including small sample size and some with no comparative group.

Animal Data

Subcutaneous reproduction and teratology studies have been performed with another insulin glargine product and with regular human insulin in rats and Himalayan rabbits. This other insulin glargine product was given to female rats before mating, during mating, and throughout pregnancy at dose up to 0.36 mg/kg/day, which is approximately 7 times the recommended human subcutaneous starting dose of 10 units/day (0.008 mg/kg/day) based on mg/m^2. In rabbits, doses of 0.072 mg/kg/day, which is approximately 2 times the recommended human subcutaneous starting dose of 10 units/day (0.008 mg/kg/day), based on mg/m^2, were administered during organogenesis. The effects of this other insulin glargine product did not generally differ from those observed with regular human insulin in rats and rabbits. However, in rabbits, five fetuses from two litters of the high-dose group exhibited dilation of the cerebral ventricles. Fertility and early embryonic development appeared normal.

8.2 Lactation

Risk Summary

There are no data on the presence of insulin glargine in human milk, the effects on the breastfed infant, or the effects on milk production. Endogenous insulin is present in human milk.

The developmental and health benefits of breastfeeding should be considered along with the mother's clinical need for BASAGLAR and any potential adverse effects on the breastfed child from BASAGLAR or from the underlying maternal condition.

8.4 Pediatric Use

The safety and effectiveness of BASAGLAR have been established in pediatric patients (age 6 to 15 years) with type 1 diabetes based on an adequate and well-controlled trial of another insulin glargine product, 100 units/mL, in pediatric patients (age 6 to 15 years) with type 1 diabetes and additional data in adults with type 1 diabetes [see Clinical Studies (14.2)]. The safety and effectiveness of BASAGLAR in pediatric patients younger than 6 years of age with type 1 diabetes and pediatric patients with type 2 diabetes has not been established.

In the pediatric clinical trial, pediatric patients (age 6 to 15 years) with type 1 diabetes had a higher incidence of severe symptomatic hypoglycemia compared to the adults in trials with type 1 diabetes [see Adverse Reactions (6.1)].

8.5 Geriatric Use

Of the total number of subjects in clinical studies of patients with type 2 diabetes who were treated with BASAGLAR or another insulin glargine product, 100 units/mL, each in combination with oral agents in a controlled clinical trial environment, 28.3% were 65 and over, while 4.5% were 75 and over. No overall differences in safety or effectiveness were observed between these subjects and younger subjects, and other reported clinical experience has not identified differences in responses between the elderly and younger patients, but greater sensitivity of some older individuals cannot be ruled out.

Nevertheless, caution should be exercised when BASAGLAR is administered to geriatric patients. In elderly patients with diabetes, the initial dosing, dose increments, and maintenance dosage should be conservative to avoid hypoglycemic reactions. Hypoglycemia may be difficult to recognize in the elderly.

8.6 Renal Impairment

The effect of renal impairment on the pharmacokinetics of BASAGLAR has not been studied. Some studies with human insulin have shown increased circulating levels of insulin in patients with renal failure. Frequent glucose monitoring and dose adjustment may be necessary for BASAGLAR in patients with renal impairment [see Warnings and Precautions (5.3)].

8.7 Hepatic Impairment

The effect of hepatic impairment on the pharmacokinetics of BASAGLAR has not been studied. However, as with all insulin products, more frequent glucose monitoring and dose adjustment may be necessary for BASAGLAR in patients with hepatic impairment [see Warnings and Precautions (5.3)].

10 OVERDOSAGE

Excess insulin administration relative to food intake, energy expenditure, or both may lead to severe and sometimes prolonged and life-threatening hypoglycemia and hypokalemia [see Warnings and Precautions (5.3, 5.6)]. Mild episodes of hypoglycemia can be treated with oral glucose. Adjustments in drug dosage, meal patterns, or physical activity level may be needed. More severe episodes with coma, seizure, or neurologic impairment may be treated with a glucagon product for emergency use or concentrated intravenous glucose. Sustained carbohydrate intake and observation may be necessary because hypoglycemia may recur after apparent clinical recovery. Hypokalemia must be corrected appropriately.

11 DESCRIPTION

Insulin glargine is a long-acting human insulin analog produced by recombinant DNA technology utilizing a non-pathogenic laboratory strain of Escherichia coli (K12) as the production organism. Insulin glargine differs from human insulin in that the amino acid asparagine at position A21 is replaced by glycine and two arginines are added to the C-terminus of the B-chain. Chemically, insulin glargine is 21A-Gly-30B-a-L-Arg-30Bb-L-Arg-human insulin and has the empirical formula C267H404N72O78S6 and a molecular weight of 6.063 kDa. Insulin glargine has the following structural formula:

BASAGLAR (insulin glargine) injection is a sterile clear and colorless aqueous solution for subcutaneous use. Each mL contains 100 units of insulin glargine (3.6378 mg).

The 3 mL BASAGLAR prefilled pen presentations contain the following inactive ingredients per mL: glycerin (17 mg), metacresol (2.7 mg), zinc oxide (content adjusted to provide 30 mcg zinc ion), and Water for Injection, USP.

The pH is adjusted by addition of aqueous solutions of hydrochloric acid 10% and/or sodium hydroxide 10%. BASAGLAR has a pH of approximately 4.

12 CLINICAL PHARMACOLOGY

12.1 Mechanism of Action

The primary activity of insulin, including insulin glargine, is regulation of glucose metabolism. Insulin and its analog lower blood glucose by stimulating peripheral glucose uptake, especially by skeletal muscle and fat, and by inhibiting hepatic glucose production. Insulin inhibits lipolysis and proteolysis, and enhances protein synthesis.

12.2 Pharmacodynamics

The pharmacodynamic profile for BASAGLAR was determined after subcutaneous administration of a single 0.5 U/kg dose in a euglycemic clamp study conducted in 91 healthy subjects. The median time to maximum effect of BASAGLAR (measured by the peak rate of glucose infusion) was approximately 12.0 hours. The pharmacodynamic profile of BASAGLAR following subcutaneous injection demonstrated sustained glucose lowering activity over 24 hours with no pronounced peak. The mean area under the glucose infusion rate curves (measure of overall pharmacodynamic effect) and maximum glucose infusion rate were 1670 mg/kg and 2.12 mg/kg/min, respectively.

A euglycemic clamp study in 20 patients with type 1 diabetes showed a similar pharmacodynamic profile with a sustained glucose lowering activity over 24 hours following a single 0.3 U/kg subcutaneous dose of BASAGLAR.

After subcutaneous injection of 0.3 units/kg of another insulin glargine product, 100 units/mL, in patients with type 1 diabetes, the duration of action after abdominal, deltoid, or thigh subcutaneous administration was similar.

The time course of action of insulins, including insulin glargine, may vary between individuals and within the same individual.

12.3 Pharmacokinetics

Absorption and Bioavailability

The pharmacokinetic profile for BASAGLAR was determined after subcutaneous administration of a single 0.5 U/kg dose in a euglycemic clamp study conducted in 91 healthy subjects. The insulin serum concentrations indicated a slow and prolonged absorption and a relatively constant concentration/time profile over 24 hours with no pronounced peak.

The median time to maximum serum insulin concentration was 12 hours after injection. On average, serum insulin concentrations declined to baseline by approximately 24 hours. The mean observed area under the serum insulin concentration-time curve from time zero to 24 hours and peak serum insulin concentration were 1720 pmol*hr/L and 103 pmol/L, respectively.

Metabolism and Elimination

After subcutaneous injection of another insulin glargine product, 100 units/mL, in diabetic patients, insulin glargine is metabolized at the carboxyl terminus of the Beta chain with formation of two active metabolites M1 (21A-Gly-insulin) and M2 (21A-Gly-des-30B-Thr-insulin). The in vitro activity of M1 and M2 were similar to that of insulin.

Specific Populations

Age, Race, and Gender: Effect of age, race, and gender on the pharmacokinetics of BASAGLAR has not been evaluated.

Obesity: Effect of BMI on the pharmacokinetics of BASAGLAR has not been evaluated.

13 NONCLINICAL TOXICOLOGY

13.1 Carcinogenesis, Mutagenesis, Impairment of Fertility

In mice and rats, standard two-year carcinogenicity studies with another insulin glargine product were performed at doses up to 0.455 mg/kg, which was for the rat approximately 10 times and for the mouse approximately 5 times the recommended human subcutaneous starting dose of 10 units/day (0.008 mg/kg/day), based on mg/m^2. The findings in female mice were not conclusive due to excessive mortality in all dose groups during the study. Histiocytomas were found at injection sites in male rats (statistically significant) and male mice (not statistically significant) in acid vehicle containing groups. These tumors were not found in female animals, in saline control, or insulin comparator groups using a different vehicle. The relevance of these findings to humans is unknown.

Another insulin glargine product was not mutagenic in tests for detection of gene mutations in bacteria and mammalian cells (Ames- and HGPRT-test) and in tests for detection of chromosomal aberrations (cytogenetics in vitro in V79 cells and in vivo in Chinese hamsters).

In a combined fertility and prenatal and postnatal study of another insulin glargine product in male and female rats at subcutaneous doses up to 0.36 mg/kg/day, which was approximately 7 times the recommended human subcutaneous starting dose of 10 units/day (0.008 mg/kg/day), based on mg/m^2, maternal toxicity due to dose-dependent hypoglycemia, including some deaths, was observed. Consequently, a reduction of the rearing rate occurred in the high-dose group only. Similar effects were observed with NPH insulin.

14 CLINICAL STUDIES

14.1 Overview of Clinical Studies

The safety and effectiveness of another insulin glargine product, 100 units/mL, given once-daily at bedtime was compared to that of once-daily and twice-daily NPH insulin in open-label, randomized, active-controlled, parallel studies of 2,327 adults and 349 pediatric patients with type 1 diabetes mellitus and 1,563 adult patients with type 2 diabetes mellitus (see Tables 8, 9, 11, and 12). In general, the reduction in glycated hemoglobin (HbA1c) with this other insulin glargine product was similar to that with NPH insulin.

14.2 Clinical Studies in Adult and Pediatric Patients with Type 1 Diabetes

Patients with inadequately controlled type 1 diabetes participated in a 24-week open-label, active-controlled study with a 28 week extension to evaluate the glucose lowering effect of once-daily BASAGLAR compared to that of once-daily administration of another insulin glargine product, 100 units/mL, or a non-U.S.-licensed insulin glargine, 100 units/mL, (comparator insulin glargine products, 100 units/mL) both in combination with mealtime insulin lispro. Randomized were 535 adults with type 1 diabetes. Mean age was 41.2 years and mean duration of diabetes was 16.39 years. 57.9% were male. 74.5% were Caucasian, 2.1% Black or African American and 4.3% American Indian or Alaskan native. 3.9% were Hispanic. 73.5 percent of patients had GFR>90 mL/min/1.73m^2. The mean BMI was approximately 25.54 kg/m^2. At week 24, treatment with BASAGLAR provided a mean reduction in HbA1c that was non-inferior to that achieved with comparator insulin glargine products, 100 units/mL (see Table 7).

Table 7: Type 1 Diabetes Mellitus – Adult (BASAGLAR plus Mealtime insulin versus Comparator Insulin Glargine Products, 100 units/mL, plus Mealtime Insulin)
Efficacy Parameter | BASAGLAR + insulin lispro (N=268 a) | Comparator Insulin Glargine Products, 100 units/mLb + insulin lispro (N=267)
HbA 1c (%)
Baseline (mean) | 7.75 | 7.79
Change from baseline (adjusted meanc,d) | -0.35 | -0.46
Difference from comparator (adjusted meanc,d) (95% CI) | 0.11 (-0.002, 0.219)
Proportion of patients achieving HbA1c <7%d | 34.5% | 32.2%
a One patient randomized to the BASAGLAR group was not included in the Full Analysis Set.
b “Comparator insulin glargine products, 100 units/mL” refers to another insulin glargine product, 100 units/mL, and a non-U.S.-licensed insulin glargine, 100 units/mL, used in this study.
c ANCOVA Model includes treatment, country and time of baseline basal insulin injection (daytime or evening/bedtime) as fixed effects and baseline HbA1c as covariate.
d The results were calculated based on the number of patients in the Full Analysis Set using their last observed post-baseline value of HbA1c. Observed HbA1c data at 24 weeks were available from 256 (95.5%) and 258 (96.6%) subjects randomized to the BASAGLAR and comparator insulin glargine products, 100 units/mL, groups, respectively.

In two clinical studies (Studies A and B), patients with type 1 diabetes (Study A; n=585, Study B; n=534) were randomized to 28 weeks of basal-bolus treatment with another insulin glargine product, 100 units/mL, or NPH insulin. Regular human insulin was administered before each meal. This other insulin glargine product was administered at bedtime. NPH insulin was administered once daily at bedtime or in the morning and at bedtime when used twice daily. In Study A, the average age was 39.2 years. The majority of patients were Caucasian (99%) and 55.7% were male. The mean BMI was approximately 24.9 kg/m^2. The mean duration of diabetes was 15.5 years. In Study B, the average age was 38.5 years. The majority of patients were Caucasian (95.3%) and 50.6% were male. The mean BMI was approximately 25.8 kg/m^2. The mean duration of diabetes was 17.4 years.

In another clinical study (Study C), patients with type 1 diabetes (n=619) were randomized to 16 weeks of basal-bolus treatment with another insulin glargine product, 100 units/mL, or NPH insulin. Insulin lispro was used before each meal. This other insulin glargine product was administered once daily at bedtime and NPH insulin was administered once or twice daily. The average age was 39.2 years. The majority of patients were Caucasian (96.9%) and 50.6% were male. The mean BMI was approximately 25.6 kg/m^2. The mean duration of diabetes was 18.5 years.

In these 3 studies, another insulin glargine product, 100 units/mL, and NPH insulin had similar effects on HbA1c (see Table 8) with a similar overall rate of hypoglycemia [see Adverse Reactions (6.1)].

Table 8: Type 1 Diabetes Mellitus – Adult (Another Insulin Glargine Product, 100 units/mL, versus NPH)
Treatment duration Treatment in combination with | Study A 28 weeks Regular insulin |  |  | Study B 28 weeks Regular insulin |  | Study C 16 weeks Insulin lispro
Treatment duration Treatment in combination with | Another Insulin Glargine Product |  | NPH | Another Insulin Glargine Product | NPH | Another Insulin Glargine Product | NPH
Number of subject treated | 292 |  | 293 | 264 | 270 | 310 | 309
HbA 1c (%)
Baseline (mean) | 8.0 |  | 8.0 | 7.7 | 7.7 | 7.6 | 7.7
Adjusted mean change at trial end | +0.2 |  | +0.1 | -0.2 | -0.2 | -0.1 | -0.1
Treatment Difference (95% CI) | +0.1 (0.0; + 0.2) |  |  | +0.1(-0.1; + 0.2) |  | 0.0 (+0.1; + 0.1)
Fasting blood glucose (mg/dL)
Baseline (mean) | 167 | 166 |  | 166 | 175 | 175 | 173
Adjusted mean change at trial end | -21 | -16 |  | -20 | -17 | -29 | -12

Type 1 Diabetes – Pediatric (see Table 9)

The efficacy of BASAGLAR to improve glycemic control in pediatric patients with type 1 diabetes mellitus is based on an adequate and well-controlled trial of another insulin glargine product, 100 units/mL, in pediatric patients with type 1 diabetes mellitus (Study D). In this randomized, active-controlled clinical study (Study D), pediatric patients (age range 6 to 15 years) with type 1 diabetes (n=349) were treated for 28 weeks with a basal-bolus insulin regimen where regular human insulin was used before each meal. Patients were randomized to either this other insulin glargine product administered once daily at bedtime or NPH insulin administered once or twice daily. The average age was 11.7 years. The majority of patients were Caucasian (96.8%) and 51.9% were male. The mean BMI was approximately 18.9 kg/m^2. The mean duration of diabetes was 4.8 years. Similar effects on HbA1c (see Table 9) were observed in both treatment groups.

Table 9: Type 1 Diabetes Mellitus – Pediatric (Another Insulin Glargine Product, 100 units/mL, plus Regular Insulin versus NPH plus Regular Insulin)
 | Study D
 | Another Insulin Glargine Product + Regular Insulin | NPH + Regular Insulin
Number of subjects treated | 174 | 175
HbA 1c
Baseline mean | 8.5 | 8.8
Change from baseline (adjusted mean) | +0.3 | +0.3
Difference from NPH (adjusted mean) (95% CI) | 0.0 (-0.2; +0.3)
Fasting blood glucose (mg/dL)
Baseline mean | 194 | 191
Mean change from baseline | -23 | -12

14.3 Clinical Studies in Adults with Type 2 Diabetes

Patients with type 2 diabetes participated in a double-blind, active-controlled study to evaluate the glucose lowering effect of once-daily BASAGLAR plus oral antidiabetic medication (OAM) compared to that of another insulin glargine product, 100 units/mL, or a non-U.S.-licensed insulin glargine, 100 units/mL (comparator insulin glargine products, 100 units/mL) administered once-daily along with OAMs. Patients were either insulin naïve (approximately 60%) and had failed to achieve adequate glycemic control on at least 2 OAMs, or were already on another insulin glargine product, 100 units/mL, or a non-U.S.-licensed insulin glargine, 100 units/mL, along with at least 2 OAMs with adequate or inadequate glycemic control (approximately 40%). A total of 759 patients were randomized. Three patients randomized to BASAGLAR did not receive study drug and were not included in efficacy analysis. The average age was approximately 59 years. The majority of patients were White (78%) and 50% of the patients were male. Sixty-eight percent of patients had GFR>90 mL/min/1.73m^2. The mean BMI was approximately 32 kg/m^2. At week 24, treatment with BASAGLAR provided a mean reduction in HbA1c that was non-inferior to that achieved with comparator insulin glargine products, 100 units/mL (see Table 10).

Table 10: Type 2 Diabetes Mellitus – Adult (BASAGLAR plus Oral Antidiabetic Medications versus Comparator Insulin Glargine Products, 100 units/mL, plus Oral Antidiabetic Medications)
 | BASAGLAR + Oral Antidiabetic Medication (N=376) a | Comparator Insulin Glargine Products, 100 units/mLb + Oral Antidiabetic Medication (N=380)
HbA 1c (%)
Baseline (mean) | 8.35 | 8.31
Change from baseline (adjusted meanc,d) | -1.3 | -1.3
Difference from comparator (adjusted meanc,d) (95% CI) | 0.05 (-0.07, 0.17)
Proportion of patients achieving HbA1c <7%d | 48.8% | 52.5%
a Three patients randomized to BASAGLAR did not receive study drug and were not included in the Full Analysis Set.
b “Comparator insulin glargine products, 100 units/mL” refers to another insulin glargine product, 100 units/mL, and a non-U.S.-licensed insulin glargine, 100 units/mL, used in this study.
c ANCOVA Model includes treatment, country, sulfonylurea use and time of baseline basal insulin injection (daytime or evening/bedtime) as fixed effects and baseline HbA1c as covariate.
d The results were calculated based on the number of patients in the Full Analysis Set using their last observed post-baseline value of HbA1c. Observed HbA1c data at 24 weeks were available from 331 (88%) and 329 (87%) subjects randomized to the BASAGLAR and comparator insulin glargine products, 100 units/mL, groups, respectively.

In a randomized, controlled clinical study (Study E) (n=570), another insulin glargine product, 100 units/mL, was evaluated for 52 weeks in combination with oral anti-diabetic medications (a sulfonylurea, metformin, acarbose, or combination of these drugs). The average age was 59.5 years. The majority of patients were Caucasian (92.8%) and 53.7% were male. The mean BMI was approximately 29.1 kg/m^2. The mean duration of diabetes was 10.3 years. This other insulin glargine product administered once daily at bedtime was as effective as NPH insulin administered once daily at bedtime in reducing HbA1c and fasting glucose (see Table 11). The rate of hypoglycemia was similar in this other insulin glargine product and NPH insulin treated patients [see Adverse Reactions (6.1)].

In a randomized, controlled clinical study (Study F), in patients with type 2 diabetes not using oral anti-diabetic medications (n=518), a basal-bolus regimen of another insulin glargine product, 100 units/mL, once daily at bedtime or NPH insulin administered once or twice daily was evaluated for 28 weeks. Regular human insulin was used before meals, as needed. The average age was 59.3 years. The majority of patients were Caucasian (80.7%) and 60% were male. The mean BMI was approximately 30.5 kg/m^2. The mean duration of diabetes was 13.7 years. This other insulin glargine product had similar effectiveness as either once- or twice daily NPH insulin in reducing HbA1c and fasting glucose (see Table 11) with a similar incidence of hypoglycemia [see Adverse Reactions (6.1)].

In a randomized, controlled clinical study (Study G), patients with type 2 diabetes were randomized to 5 years of treatment with another insulin glargine product, 100 units/mL, once-daily or twice-daily NPH insulin. For patients not previously treated with insulin, the starting dose of this other insulin glargine product or NPH insulin was 10 units daily. Patients who were already treated with NPH insulin either continued on the same total daily NPH insulin dose or started this other insulin glargine product at a dose that was 80% of the total previous NPH insulin dose. The primary endpoint for this study was a comparison of the progression of diabetic retinopathy by 3 or more steps on the ETDRS scale. HbA1c change from baseline was a secondary endpoint. Similar glycemic control in the 2 treatment groups was desired in order to not confound the interpretation of the retinal data. Patients or study personnel used an algorithm to adjust this other insulin glargine product and NPH insulin doses to a target fasting plasma glucose ≤100 mg/dL. After this other insulin glargine product or NPH insulin dose was adjusted, other anti-diabetic agents, including pre-meal insulin were to be adjusted or added. The average age was 55.1 years. The majority of patients were Caucasian (85.3%) and 53.9% were male. The mean BMI was approximately 34.3 kg/m^2. The mean duration of diabetes was 10.8 years. This other insulin glargine product group had a smaller mean reduction from baseline in HbA1c compared to the NPH insulin group, which may be explained by the lower daily basal insulin doses in this other insulin glargine product group (see Table 11). Both treatment groups had a similar incidence of reported symptomatic hypoglycemia. The incidence of severe symptomatic hypoglycemia in the ORIGIN Trial is given in Table 5 [see Adverse Reactions (6.1)].

Table 11: Type 2 Diabetes Mellitus – Adult (Another Insulin Glargine Product, 100 units/mL, versus NPH)
Treatment duration Treatment in combination with | Study E 52 weeks Oral agents |  | Study F 28 weeks Regular insulin |  | Study G 5 years Regular insulin
Treatment duration Treatment in combination with | Another Insulin Glargine Product | NPH | Another Insulin Glargine Product | NPH | Another Insulin Glargine Product | NPH
Number of subjects treated | 289 | 281 | 259 | 259 | 513 | 504
HbA 1c
Baseline mean | 9.0 | 8.9 | 8.6 | 8.5 | 8.4 | 8.3
Adjusted mean change from baseline | -0.5 | -0.4 | -0.4 | -0.6 | -0.6 | -0.8
Another insulin glargine product, 100 units/mL – NPH | -0.1 |  | +0.2 |  | +0.2
95% CI for Treatment difference | (-0.3; +0.1) |  | (0.0; +0.4) |  | (+0.1; +0.4)
Fasting blood glucose (mg/dL)
Baseline mean | 179 | 180 | 164 | 166 | 190 | 180
Adjusted mean change from baseline | -49 | -46 | -24 | -22 | -45 | -44

Another Insulin Glargine Product, 100 units/mL, Timing of Daily Dosing (see Table 12)

The safety and efficacy of this other insulin glargine product administered pre-breakfast, pre-dinner, or at bedtime were evaluated in a randomized, controlled clinical study in patients with type 1 diabetes (Study H; n=378). Patients were also treated with insulin lispro at mealtime. The average age was 40.9 years. All patients were Caucasian (100%) and 53.7% were male. The mean BMI was approximately 25.3 kg/m^2. The mean duration of diabetes was 17.3 years. This other insulin glargine product administered at different times of the day resulted in similar reductions in HbA1c compared to that with bedtime administration (see Table 12). In these patients, data are available from 8-point home glucose monitoring. The maximum mean blood glucose was observed just prior to injection of this other insulin glargine product regardless of time of administration.

In this study, 5% of patients in this other insulin glargine product-breakfast arm discontinued treatment because of lack of efficacy. No patients in the other two arms discontinued for this reason. The safety and efficacy of this other insulin glargine product administered pre-breakfast or at bedtime were also evaluated in a randomized, active-controlled clinical study (Study I, n=697) in patients with type 2 diabetes not adequately controlled on oral anti-diabetic therapy. All patients in this study also received glimepiride 3 mg daily. The average age was 60.8 years. The majority of patients were Caucasian (96.6%) and 53.7% were male. The mean BMI was approximately 28.7 kg/m^2. The mean duration of diabetes was 10.1 years. This other insulin glargine product given before breakfast was at least as effective in lowering HbA1c as this other insulin glargine product given at bedtime or NPH insulin given at bedtime (see Table 12).

Table 12: Type 1 Diabetes Mellitus – Adults (Another Insulin Glargine Product, 100 units/mL, plus Insulin Lispro) and Type 2 Diabetes Mellitus – Adults (Another Insulin Glargine Product, 100 units/mL, plus Glimepiride versus NPH plus Glimepiride)
Treatment duration Treatment in combination with | Study H 24 weeks Insulin lispro |  |  | Study I 24 weeks Glimepiride
Treatment duration Treatment in combination with | Another Insulin Glargine Product Breakfast | Another Insulin Glargine Product Dinner | Another Insulin Glargine Product Bedtime | Another Insulin Glargine Product Breakfast | Another Insulin Glargine Product Bedtime | NPH Bedtime
Number of subjects treateda | 112 | 124 | 128 | 234 | 226 | 227
HbA 1c
Baseline mean | 7.6 | 7.5 | 7.6 | 9.1 | 9.1 | 9.1
Mean change from baseline | -0.2 | -0.1 | 0.0 | -1.3 | -1.0 | -0.8
a Intent to treat.
b Total number of patients evaluable for safety.
c Not applicable.

Five-year Trial Evaluating the Progression of Retinopathy

Retinopathy was evaluated in clinical studies with another insulin glargine product, 100 units/mL, by analysis of reported retinal adverse events and fundus photography. The numbers of retinal adverse events reported for this other insulin glargine product and NPH insulin treatment groups were similar for patients with type 1 and type 2 diabetes.

Another insulin glargine product, 100 units/mL, was compared to NPH insulin in a 5-year randomized clinical trial that evaluated the progression of retinopathy as assessed with fundus photography using a grading protocol derived from the Early Treatment Diabetic Retinopathy Scale (ETDRS). Patients had type 2 diabetes (mean age 55 years) with no (86%) or mild (14%) retinopathy at baseline. Mean baseline HbA1c was 8.4%. The primary outcome was progression by 3 or more steps on the ETDRS scale at study endpoint. Patients with pre-specified post-baseline eye procedures (pan-retinal photocoagulation for proliferative or severe nonproliferative diabetic retinopathy, local photocoagulation for new vessels, and vitrectomy for diabetic retinopathy) were also considered as 3-step progressions regardless of actual change in ETDRS score from baseline. Retinopathy graders were blinded to treatment group assignment. The results for the primary endpoint are shown in Table 13 for both the per-protocol and Intent-to-Treat populations, and indicate similarity of this other insulin glargine product to NPH in the progression of diabetic retinopathy as assessed by this outcome.

Table 13: Number (%) of Patients with 3 or More Step Progression on ETDRS Scale at Endpoint
 | Another Insulin Glargine Product, 100 units/mL (%) | NPH (%) | Differencea,b (SE) | 95% CI for difference
Per-protocol | 53/374 (14.2%) | 57/363 (15.5%) | -2.0% (2.6%) | -7.0% to +3.1%
Intent-to-Treat | 63/502 (12.5%) | 71/487 (14.6%) | -2.1% (2.1%) | -6.3% to +2.1%
a Difference = another insulin glargine product, 100 units/mL – NPH.
b Using a generalized linear model (SAS GENMOD) with treatment and baseline HbA1c strata (cutoff 9.0%) as the classified independent variables, and with binomial distribution and identity link function.

The ORIGIN Study

The Outcome Reduction with Initial Glargine Intervention trial (i.e., ORIGIN) was an open-label, randomized, 2-by-2, factorial design study. One intervention in ORIGIN compared the effect of another insulin glargine product, 100 units/mL, to standard care on major adverse cardiovascular outcomes in 12,537 participants ≥50 years of age with abnormal glucose levels [i.e., impaired fasting glucose (IFG) and/or impaired glucose tolerance (IGT)] or early type 2 diabetes mellitus and established cardiovascular (i.e., CV) disease or CV risk factors at baseline.

The objective of the trial was to demonstrate that use of this other insulin glargine product could significantly lower the risk of major cardiovascular outcomes compared to standard care. Two co-primary composite cardiovascular endpoints were used in ORIGIN. The first co-primary endpoint was the time to first occurrence of a major adverse cardiovascular event defined as the composite of CV death, nonfatal myocardial infarction and nonfatal stroke. The second co-primary endpoint was the time to the first occurrence of CV death or nonfatal myocardial infarction or nonfatal stroke or revascularization procedure or hospitalization for heart failure.

Participants were randomized to either this other insulin glargine product (N=6264) titrated to a goal fasting plasma glucose of ≤95 mg/dL or to standard care (N=6273). Anthropometric and disease characteristics were balanced at baseline. The mean age was 64 years and 8% of participants were 75 years of age or older. The majority of participants were male (65%). Fifty nine percent were Caucasian, 25% were Latin, 10% were Asian and 3% were Black. The median baseline BMI was 29 kg/m^2. Approximately 12% of participants had abnormal glucose levels (IGT and/or IFG) at baseline and 88% had type 2 diabetes. For patients with type 2 diabetes, 59% were treated with a single oral antidiabetic drug, 23% had known diabetes but were on no antidiabetic drug and 6% were newly diagnosed during the screening procedure. The mean HbA1c (SD) at baseline was 6.5% (1.0). Fifty nine percent of participants had had a prior cardiovascular event and 39% had documented coronary artery disease or other cardiovascular risk factors.

Vital status was available for 99.9% and 99.8% of participants randomized to this other insulin glargine product and standard care respectively at end of trial. The median duration of follow-up was 6.2 years [range: 8 days to 7.9 years]. The mean HbA1c (SD) at the end of the trial was 6.5% (1.1) and 6.8% (1.2) in this other insulin glargine product and standard group respectively. The median dose of this other insulin glargine product at end of trial was 0.45 U/kg. Eighty-one percent of patients randomized to this other insulin glargine product were using this other insulin glargine product at end of the study. The mean change in body weight from baseline to the last treatment visit was 2.2 kg greater in this other insulin glargine group than in the standard care group.

Overall, the incidence of major adverse cardiovascular outcomes was similar between groups (see Table 14). All-cause mortality was also similar between groups.

Table 14: Cardiovascular Outcomes in ORIGIN – Time to First Event Analyses
 | Another Insulin Glargine Product, 100 units/mL N=6264 | Standard Care N=6273 | Another Insulin Glargine Product, 100 units/mL vs. Standard Care
 | n (Events per 100 PY) | n (Events per 100 PY) | Hazard Ratio (95% CI)
Co-primary endpoints
CV death, nonfatal myocardial infarction, or nonfatal stroke | 1041 (2.9) | 1013 (2.9) | 1.02 (0.94, 1.11)
CV death, nonfatal myocardial infarction, nonfatal stroke, hospitalization for heart failure or revascularization procedure | 1792 (5.5) | 1727 (5.3) | 1.04 (0.97, 1.11)
Components of co-primary endpoints
CV death | 580 | 576 | 1.00 (0.89, 1.13)
Myocardial Infarction (fatal or nonfatal) | 336 | 326 | 1.03 (0.88, 1.19)
Stroke (fatal or nonfatal) | 331 | 319 | 1.03 (0.89, 1.21)
Revascularizations | 908 | 860 | 1.06 (0.96, 1.16)
Hospitalization for heart failure | 310 | 343 | 0.90 (0.77, 1.05)

In the ORIGIN trial, the overall incidence of cancer (all types combined) or death from cancer in the ORIGIN trial (see Table 15) was similar between treatment groups.

Table 15: Cancer Outcomes in ORIGIN – Time to First Event Analyses
 | Another Insulin Glargine Product, 100 units/mL N=6264 | Standard Care N=6273 | Another Insulin Glargine Product, 100 units/mL vs. Standard Care
 | n (Events per 100 PY) | n (Events per 100 PY) | Hazard Ratio (95% CI)
Cancer endpoints
Any cancer event (new or recurrent) | 559 (1.56) | 561 (1.56) | 0.99 (0.88, 1.11)
New cancer events | 524 (1.46) | 535 (1.49) | 0.96 (0.85, 1.09)
Death due to Cancer | 189 (0.51) | 201 (0.54) | 0.94 (0.77, 1.15)

16 HOW SUPPLIED/STORAGE AND HANDLING

16.1 How Supplied

BASAGLAR (insulin glargine) injection is a clear, colorless solution, 100 units/mL (U-100), available as:

BASAGLAR | Total Volume | NDC Number | Package Size
BASAGLAR single-patient-use KwikPen | 3 mL | 0002-7715-59 | 5 pens
BASAGLAR single-patient-use Tempo Pena | 3 mL | 0002-8214-05 | 5 pens
a Tempo Pen contains a component that allows for data connectivity when used with a compatible transmitter.

The BASAGLAR KwikPen and Tempo Pen dial in 1 unit increments.

Needles are not included.

This device is recommended for use with Becton, Dickinson & Company's insulin pen needles which are sold separately.

16.2 Storage and Handling

Dispense in the original sealed carton with the enclosed Instructions for Use.

Protect BASAGLAR from heat and light. Do not freeze BASAGLAR.

In-use BASAGLAR prefilled pens must be used within 28 days or be discarded, even if they still contain BASAGLAR.

Storage conditions are summarized in the following table:

 | Not In-Use (Unopened) Room Temperature (up to 86°F [30°C]) | Not In-Use (Unopened) Refrigerated (36°F to 46°F [2°C to 8°C]) | In-Use (Opened) Room Temperature, (up to 86°F [30°C])
3 mL single-patient-use BASAGLAR KwikPen | 28 days | Until expiration date | 28 days, Do not refrigerate.
3 mL single-patient-use BASAGAR Tempo Pen | 28 days | Until expiration date | 28 days, Do not refrigerate.

17 PATIENT COUNSELING INFORMATION

See FDA-approved patient labeling (Patient Information and Instructions for Use).

Never Share a BASAGLAR Prefilled Pen Between Patients

Advise patients that they must never share a BASAGLAR prefilled pen with another person, even if the needle is changed, because doing so carries a risk for transmission of blood-borne pathogens [see Warnings and Precautions (5.1)].

Hyperglycemia or Hypoglycemia

Inform patients that hypoglycemia is the most common adverse reaction with insulin. Inform patients of the symptoms of hypoglycemia. Inform patients that the ability to concentrate and react may be impaired as a result of hypoglycemia. This may present a risk in situations where these abilities are especially important, such as driving or operating other machinery. Advise patients who have frequent hypoglycemia or reduced or absent warning signs of hypoglycemia to use caution when driving or operating machinery.

Advise patients that changes in insulin regimen can predispose to hyperglycemia or hypoglycemia and that changes in insulin regimen should be made under close medical supervision [see Warnings and Precautions (5.2)].

Medication errors

Inform patients to always check the insulin label before each injection [see Warnings and Precautions (5.4)].

Literature revised July 2021

Manufactured by: Eli Lilly and Company
Indianapolis, IN 46285, USA
US License Number 1891

Copyright © 2015, 2021, Eli Lilly and Company. All rights reserved.

BAS-0007-USPI-20210727

Patient Information
BASAGLAR® (baz-a-glar)
(insulin glargine)
injection, for subcutaneous use
100 units/mL (U-100)

Do not share your BASAGLAR prefilled pen with other people, even if the needle has been changed. You may give other people a serious infection, or get a serious infection from them.
What is BASAGLAR?

- BASAGLAR is a long-acting man made insulin used to control high blood sugar in adults and children with type 1 diabetes mellitus and adults with type 2 diabetes mellitus.
- BASAGLAR is not for use to treat diabetic ketoacidosis.
- It is not known if BASAGLAR is safe and effective in children less than 6 years of age with type 1 diabetes mellitus or in children with type 2 diabetes mellitus.

Who should not use BASAGLAR?
Do not use BASAGLAR if you:

- are having an episode of low blood sugar (hypoglycemia).
- have an allergy to insulin glargine or any of the ingredients in BASAGLAR. See the end of this Patient Information leaflet for a complete list of ingredients in BASAGLAR.

What should I tell my healthcare provider before using BASAGLAR?
Before using BASAGLAR, tell your healthcare provider about all your medical conditions, including if you:

- have liver or kidney problems.
- take any other medicines, especially ones commonly called TZDs (thiazolidinediones).
- have heart failure or other heart problems. If you have heart failure, it may get worse while you take TZDs with BASAGLAR.
- are pregnant, planning to become pregnant, or are breastfeeding. It is not known if BASAGLAR may harm your unborn or breastfeeding baby.

Tell your healthcare provider about all the medicines you take, including prescription and over-the-counter medicines, vitamins and herbal supplements.
Before you start using BASAGLAR, talk to your healthcare provider about low blood sugar and how to manage it.

How should I use BASAGLAR?

- Read the detailed Instructions for Use that come with your BASAGLAR.
- Use BASAGLAR exactly as your healthcare provider tells you to. Your healthcare provider should tell you how much BASAGLAR to use and when to use it.
- Know the amount of BASAGLAR you use. Do not change the amount of BASAGLAR you use unless your healthcare provider tells you to.
- Check your insulin label each time you give your injection to make sure you are using the correct insulin.
- You may take BASAGLAR at any time during the day but you must take it at the same time each day.
- Only use BASAGLAR that is clear and colorless. If your BASAGLAR is cloudy or slightly colored, return it to your pharmacy for a replacement.
- BASAGLAR is injected under the skin (subcutaneously) of your stomach area, buttocks, upper legs or upper arms. Do not use BASAGLAR in an insulin pump or inject BASAGLAR into your vein (intravenously).
- Change (rotate) your injection sites within the area you chose with each dose to reduce your risk of getting lipodystrophy (pits in skin or thickened skin) and localized cutaneous amyloidosis (skin with lumps) at the injection sites.
  - Do not use the exact same spot for each injection.
  - Do not inject where the skin has pits, is thickened, or has lumps.
  - Do not inject where the skin is tender, bruised, scaly or hard, or into scars or damaged skin.
- Do not mix BASAGLAR with any other type of insulin or liquid medicine.
- Always use a new needle for each injection to help prevent infections and blocked needles. Do not reuse or share your needles with other people. You may give other people a serious infection or get a serious infection from them.
- Check your blood sugar levels. Ask your healthcare provider what your blood sugar should be and when you should check your blood sugar levels.

Keep BASAGLAR and all medicines out of the reach of children.

Your dose of BASAGLAR may need to change because of:

- change in level of physical activity or exercise, weight gain or loss, increased stress, illness, change in diet, or because of other medicines you take.

What should I avoid while using BASAGLAR?
While using BASAGLAR do not:

- drive or operate heavy machinery, until you know how BASAGLAR affects you.
- drink alcohol or use over-the-counter medicines that contain alcohol.

What are the possible side effects of BASAGLAR?
BASAGLAR may cause serious side effects that can lead to death, including:

- low blood sugar (hypoglycemia). Signs and symptoms that may indicate low blood sugar include:
  - dizziness or light-headedness, sweating, confusion, headache, blurred vision, slurred speech, shakiness, fast heartbeat, anxiety, irritability or mood change, hunger.
- severe allergic reaction (whole body reaction). Get medical help right away if you have any of these signs or symptoms of a severe allergic reaction:
  - a rash over your whole body, trouble breathing, a fast heartbeat, or sweating.
- low potassium in your blood (hypokalemia).
- heart failure. Taking certain diabetes pills called thiazolidinediones or “TZDs” with BASAGLAR may cause heart failure in some people. This can happen even if you have never had heart failure or heart problems before. If you already have heart failure it may get worse while you take TZDs with BASAGLAR. Your healthcare provider should monitor you closely while you are taking TZDs with BASAGLAR. Tell your healthcare provider if you have any new or worse symptoms of heart failure including:
  - shortness of breath, swelling of your ankles or feet, sudden weight gain.

Treatment with TZDs and BASAGLAR may need to be changed or stopped by your healthcare provider if you have new or worse heart failure.
Get emergency medical help if you have:

- trouble breathing, shortness of breath, fast heartbeat, swelling of your face, tongue, or throat, sweating, extreme drowsiness, dizziness, confusion.

The most common side effects of BASAGLAR include:

- low blood sugar (hypoglycemia), weight gain, allergic reactions, including reactions at the injection site, skin thickening or pits at the injection site (lipodystrophy).

These are not all the possible side effects of BASAGLAR. Call your doctor for medical advice about side effects. You may report side effects to FDA at 1-800-FDA-1088 (1-800-332-1088).

General information about the safe and effective use of BASAGLAR.
Medicines are sometimes prescribed for purposes other than those listed in a Patient Information leaflet. Do not use BASAGLAR for a condition for which it was not prescribed. Do not give BASAGLAR to other people, even if they have the same symptoms that you have. It may harm them.
This Patient Information leaflet summarizes the most important information about BASAGLAR. If you would like more information, talk with your healthcare provider. You can ask your pharmacist or healthcare provider for information about BASAGLAR that is written for health professionals. For more information, go to www.basaglar.com or call 1-800-545-5979.

What are the ingredients in BASAGLAR?

- Active ingredient: insulin glargine
- Inactive ingredients: glycerin, metacresol, zinc oxide, and Water for Injection, USP as inactive ingredients. Hydrochloric acid and/or sodium hydroxide may be added to adjust the pH.

Patient Information revised: November 2023

Manufactured by: Eli Lilly and Company, Indianapolis, IN 46285 USA
US License Number 1891
Copyright © 2015, 2023, Eli Lilly and Company. All rights reserved.

This Patient Information has been approved by the U.S. Food and Drug Administration

BAS-0006-PPI-20231129

BASAGLAR KWIKPEN INSTRUCTIONS FOR USE

Instructions for Use

BASAGLAR® KwikPen®

(insulin glargine)

injection, for subcutaneous use

100 units/mL, 3 mL single-patient-use pen

Read the Instructions for Use before you start using BASAGLAR and each time you get another BASAGLAR® KwikPen®. There may be new information. This information does not take the place of talking to your healthcare provider about your medical condition or your treatment.

Do not share your BASAGLAR KwikPen with other people, even if the needle has been changed. You may give other people a serious infection or get a serious infection from them.

BASAGLAR KwikPen (“Pen”) is a disposable single-patient-use prefilled pen containing 300 units (3mL) of BASAGLAR. One pen contains multiple doses of medicine.

- Your healthcare provider will tell you how many units to give as your dose and how to inject your prescribed dose of medicine.
- You can give a dose of 1 to 80 units in a single injection.
- If your prescribed dose is more than 80 units, you will need to give yourself more than 1 injection.
- The plunger only moves a little with each injection, and you may not notice that it moves. When the plunger reaches the end of the cartridge, you have used all 300 units in the Pen.

People who are blind or have vision problems should not use the Pen without help from a person trained to use the BASAGLAR prefilled pen.

How to recognize your BASAGLAR KwikPen

- Pen color: Light grey
- Dose Knob: Light grey with green ring on the end
- Labels: Light grey with green color bars

Supplies needed to give your injection

- BASAGLAR KwikPen
- KwikPen compatible Needle (Becton, Dickinson and Company Pen Needles recommended)
- Alcohol swab

Preparing your Pen

- Wash your hands with soap and water.
- Check the Pen to make sure you are taking the right type of insulin. This is especially important if you use more than 1 type of insulin.
- Do not use your Pen past the expiration date printed on the Label or for more than 28 days after you first start using the Pen.
- Always use a new needle for each injection to help prevent infections and blocked needles. Do not reuse or share your needles with other people. You may give other people a serious infection or get a serious infection from them.

Step 1:

- Pull the Pen Cap straight off.
  - Do not remove the Pen Label.
- Wipe the Rubber Seal with an alcohol swab.

Step 2:

- Check the liquid in the Pen.
  BASAGLAR should look clear and colorless. Do not use if it is cloudy, colored, or has particles or clumps in it.

Step 3:

- Select a new Needle.
- Pull off the Paper Tab from the Outer Needle Shield.

Step 4:

- Push the capped Needle straight onto the Pen and twist the Needle on until it is tight.

Step 5:

- Pull off the Outer Needle Shield. Do not throw it away.
- Pull off the Inner Needle Shield and throw it away.

Priming your Pen

Prime before each injection.

- Priming means removing the air from the Needle and Cartridge that may collect during normal use. It is important to prime your Pen before each injection so that it will work correctly.
- If you do not prime before each injection, you may get too much or too little insulin.

Step 6:

- To prime your Pen, turn the Dose Knob to select 2 units.

Step 7:

- Hold your Pen with the Needle pointing up. Tap the Cartridge Holder gently to collect air bubbles at the top.

Step 8:

- Continue holding your Pen with Needle pointing up. Push the Dose Knob in until it stops, and “0” is seen in the Dose Window. Hold the Dose Knob in and count to 5 slowly.
  You should see insulin at the tip of the Needle.
  - If you do not see insulin, repeat the priming steps, but not more than 4 times.
  - If you still do not see insulin, change the Needle and repeat the priming steps.
    Small air bubbles are normal and will not affect your dose.

Selecting your dose

- If your dose is more than 80 units, you will need to give more than 1 injection.
  - Talk to your healthcare provider about how to give your dose.
  - Use a new Needle for each injection and repeat the priming step.

Step 9:

- Turn the Dose Knob to select the number of units you need to inject. The Dose Indicator should line up with your dose.
  - The Pen dials 1 unit at a time.
  - The Dose Knob clicks as you turn it.
  - Do not dial your dose by counting the clicks because you may dial the wrong dose.
  - The dose can be corrected by turning the Dose Knob in either direction until the correct dose lines up with the Dose Indicator.
  - The even numbers are printed on the dial.
  - The odd numbers, after the number 1, are shown as full lines.
- Always check the number in the Dose Window to make sure you have dialed the correct dose.

(Example: 12 units shown in the Dose Window)
(Example: 25 units shown in the Dose Window)

The Pen will not let you dial more than the number of units left in the Pen.

- If you need to inject more than the number of units left in the Pen, you may either:
  - inject the amount left in your Pen and then use a new Pen to give the rest of your dose, or
  - get a new Pen and inject the full dose.
- It is normal to see a small amount of insulin left in the Pen that you can not inject.

Giving your injection

- Inject your insulin as your healthcare provider has shown you.
- Change (rotate) your injection sites within the area you choose for each dose to reduce your risk of getting lipodystrophy (pits in skin or thickened skin) and localized cutaneous amyloidosis (skin with lumps) at the injection sites. Do not inject where the skin has pits, is thickened, or has lumps. Do not inject where the skin is tender, bruised, scaly or hard, or into scars or damaged skin.
- Do not try to change your dose while injecting.

Step 10:
Choose your injection site.

- BASAGLAR is injected under the skin (subcutaneously) of your stomach area, buttocks, upper legs or upper arms.
- Wipe the skin with an alcohol swab, and let the injection site dry before you inject your dose.

Step 11:

- Insert the Needle into your skin.
- Push the Dose Knob all the way in.
- Continue to hold the Dose Knob in and slowly count to 5 before removing the needle.
  Note: Do not try to inject your insulin by turning the Dose Knob. You will not receive your insulin by turning the Dose Knob.

Step 12:

- Pull the Needle out of your skin.
  - A drop of insulin at the Needle tip is normal. It will not affect your dose.
- Check the number in the Dose Window
  - If you see “0” in the Dose Window, you have received the full amount you dialed.
  - If you do not see “0” in the Dose Window you did not receive your full dose. Do not redial. Insert the needle into your skin and finish your injection.
  - If you still do not think you received the full amount you dialed for your injection, do not start over or repeat that injection. Monitor your blood glucose and call your healthcare provider for further instructions.
  - If you normally need to give 2 injections for your full dose, be sure to give your second injection.
    The plunger only moves a little with each injection, and you may not notice that it moves.
    If you see blood after you take the Needle out of your skin, press the injection site lightly with a piece of gauze or an alcohol swab. Do not rub the area.

After your injection

Step 13:

- Carefully replace the Outer Needle Shield.

Step 14:

- Unscrew the capped Needle and throw it away (see Disposing of Pens and Needles section below).
- Do not store the Pen with the Needle attached to prevent leaking, blocking the Needle, and air from entering the Pen.

Step 15:

- Replace the Pen Cap by lining up the Cap Clip with the Dose Indicator and pushing straight on.

Disposing of Pens and Needles

- Put your used needles in a FDA-cleared sharps disposal container right away after use. Do not throw away (dispose of) loose needles in your household trash.
- If you do not have a FDA-cleared sharps disposal container, you may use a household container that is:
  - made of a heavy-duty plastic,
  - can be closed with a tight-fitting, puncture-resistant lid, without sharps being able to come out,
  - upright and stable during use,
  - leak-resistant, and
  - properly labeled to warn of hazardous waste inside the container.
- When your sharps disposal container is almost full, you will need to follow your community guidelines for the right way to dispose of your sharps disposal container. There may be state or local laws about how you should throw away used needles and syringes. For more information about safe sharps disposal, and for specific information about sharps disposal in the state that you live in, go to the FDA's website at: http://www.fda.gov/safesharpsdisposal
- Do not dispose of your used sharps disposal container in your household trash unless your community guidelines permit this. Do not recycle your used sharps disposal container.
- The used Pen may be discarded in your household trash after you have removed the needle.

Storing your BASAGLAR KwikPen

Unused Pens

- Store unused Pens in the refrigerator at 36°F to 46°F (2°C to 8°C).
- Do not freeze BASAGLAR. Do not use if it has been frozen.
- Unused Pens may be used until the expiration date printed on the Label, if the Pen has been kept in the refrigerator.

In-use Pen

- Store the Pen you are currently using at room temperature [up to 86°F (30°C)] and away from heat and light.
- Throw away the Pen you are using after 28 days, even if it still has insulin left in it.

General information about the safe and effective use of your Pen

- Keep your Pen and needles out of the sight and reach of children.
- Always use a new needle for each injection.
- Do not share your Pen or needles with other people. You may give other people a serious infection or get a serious infection from them.
- Do not use your Pen if any part looks broken or damaged.
- Always carry an extra Pen in case yours is lost or damaged.

Troubleshooting

- If you can not remove the Pen Cap, gently twist the cap back and forth, and then pull the cap straight off.
- If the Dose Knob is hard to push:
  - Pushing the Dose Knob more slowly will make it easier to inject.
  - Your Needle may be blocked. Put on a new Needle and prime the Pen.
  - You may have dust, food, or liquid inside the Pen. Throw the Pen away and get a new Pen.

If you have any questions or problems with your BASAGLAR KwikPen, contact Lilly at 1-800-LillyRx (1-800- 545-5979) or call your healthcare provider for help. For more information on BASAGLAR KwikPen and insulin, go to www.basaglar.com.

Scan this code to launch www.basaglar.com

This Instructions for Use have been approved by the U.S. Food and Drug Administration. BASAGLAR® and BASAGLAR® KwikPen® are trademarks of Eli Lilly and Company.

Instructions for Use revised: November 2022

Manufactured by:

Eli Lilly and Company

Indianapolis, IN 46285, USA

US License Number 1891

Copyright © 2015, 2022, Eli Lilly and Company. All rights reserved.

BASAGLAR KwikPen meets the current dose accuracy and functional requirements of ISO 11608-1.

BASKP-0009-IFU-20221115

BASAGLAR TEMPO PEN INSTRUCTIONS FOR USE

Instructions for Use

BASAGLAR® Tempo Pen™ (insulin glargine) injection, for subcutaneous use

100 units/mL, 3 mL pen, single-patient-use

Read the Instructions for Use before you start using BASAGLAR and each time you get another BASAGLAR Tempo Pen. There may be new information. This information does not take the place of talking to your healthcare provider about your medical condition or your treatment.

Do not share your BASAGLAR Tempo Pen with other people, even if the needle has been changed. You may give other people a serious infection or get a serious infection from them.

BASAGLAR Tempo Pen (“Pen”) is a disposable single-patient-use prefilled pen containing 300 units (3mL) of BASAGLAR. One pen contains multiple doses of medicine.

- Your healthcare provider will tell you how many units to give as your dose and how to inject your prescribed dose of medicine.
- You can give a dose of 1 to 80 units in a single injection.
- If your prescribed dose is more than 80 units, you will need to give yourself more than 1 injection.
- The Plunger only moves a little with each injection, and you may not notice that it moves. When the Plunger reaches the end of the cartridge, you have used all 300 units in the Pen.

People who are blind or have vision problems should not use the Pen without help from a person trained to use the BASAGLAR prefilled pen.

This BASAGLAR Tempo Pen contains a component that allows for data connectivity when used with a compatible transmitter.

How to recognize your BASAGLAR Tempo Pen

- Pen color: Light grey
- Dose Knob: Light grey
- Labels: Light grey with green color bars

Supplies needed to give your injection

- BASAGLAR Tempo Pen
- Tempo Pen compatible Needle (Becton, Dickinson and Company Pen Needles recommended)
- Alcohol swab

Preparing your Pen

- Wash your hands with soap and water.
- Check the Pen to make sure you are taking the right type of insulin. This is especially important if you use more than 1 type of insulin.
- Do not use your Pen past the expiration date printed on the Label or for more than 28 days after you first start using the Pen.
- Always use a new needle for each injection to help prevent infections and blocked needles. Do not reuse or share your needles with other people. You may give other people a serious infection or get a serious infection from them.

Step 1:

- Pull the Pen Cap straight off.
  - Do not remove the Pen Label.
- Wipe the Rubber Seal with an alcohol swab.

Step 2:

- Check the liquid in the Pen.
  BASAGLAR should look clear and colorless. Do not use if it is cloudy, colored, or has particles or clumps in it.

Step 3:

- Select a new Needle.
- Pull off the Paper Tab from the Outer Needle Shield.

Step 4:

- Push the capped Needle straight onto the Pen and twist the Needle on until it is tight.

Step 5:

- Pull off the Outer Needle Shield. Do not throw it away.
- Pull off the Inner Needle Shield and throw it away.

Priming your Pen

Prime before each injection.

- Priming means removing the air from the Needle and Cartridge that may collect during normal use. It is important to prime your Pen before each injection so that it will work correctly.
- If you do not prime before each injection, you may get too much or too little insulin.

Step 6:

- To prime your Pen, turn the Dose Knob to select 2 units.

Step 7:

- Hold your Pen with the Needle pointing up. Tap the Cartridge Holder gently to collect air bubbles at the top.

Step 8:

- Continue holding your Pen with the Needle pointing up. Push the Dose Knob in until it stops, and “0” is seen in the Dose Window. Hold the Dose Knob in and count to 5 slowly.
  You should see insulin at the tip of the Needle.
  - If you do not see insulin, repeat the priming steps 6 to 8, but not more than 4 times.
  - If you still do not see insulin, change the Needle and repeat the priming steps 6 to 8.
  Small air bubbles are normal and will not affect your dose.

Selecting your dose

- You can give a dose of 1 to 80 units in a single injection.
- If your dose is more than 80 units, you will need to give more than 1 injection.
  - Talk to your healthcare provider about how to give your dose.
  - Use a new Needle for each injection and repeat the priming step.

Step 9:

- Turn the Dose Knob to select the number of units you need to inject. The Dose Indicator should line up with your dose.
  - The Pen dials 1 unit at a time.
  - The Dose Knob clicks as you turn it.
  - Do not dial your dose by counting the clicks because you may dial the wrong dose.
  - The dose can be corrected by turning the Dose Knob in either direction until the correct dose lines up with the Dose Indicator.
  - The even numbers are printed on the dial.
  - The odd numbers, after the number 1, are shown as full lines.
- Always check the number in the Dose Window to make sure you have dialed the correct dose.

(Example: 12 units shown in the Dose Window)
(Example: 25 units shown in the Dose Window)

- The Pen will not let you dial more than the number of units left in the Pen.
- If you need to inject more than the number of units left in the Pen, you may either:
  - inject the amount left in your Pen and then use a new Pen to give the rest of your dose, or
  - get a new Pen and inject the full dose.
- It is normal to see a small amount of insulin left in the Pen that you cannot inject.

Giving your injection

- Inject your insulin as your healthcare provider has shown you.
- Change (rotate) your injection sites within the area you choose for each dose to reduce your risk of getting lipodystrophy (pits in skin or thickened skin) and localized cutaneous amyloidosis (skin with lumps) at the injection sites. Do not inject where skin has pits, is thickened, or has lumps. Do not inject where the skin is tender, bruised, scaly or hard, or into scars or damaged skin.
- Do not try to change your dose while injecting.

Step 10:
Choose your injection site.

- BASAGLAR is injected under the skin (subcutaneously) of your stomach area, buttocks, upper legs or upper arms.
- Wipe the skin with an alcohol swab, and let the injection site dry before you inject your dose.

Step 11:

- Insert the Needle into your skin.
- Push the Dose Knob all the way in.

- Continue to hold the Dose Knob in and slowly count to 5 before removing the needle.
  Note: Do not try to inject your insulin by turning the Dose Knob. You will not receive your insulin by turning the Dose Knob.

Step 12:

- Pull the Needle out of your skin.
  - A drop of insulin at the Needle tip is normal. It will not affect your dose.
- Check the number in the Dose Window
  - If you see “0” in the Dose Window, you have received the full amount you dialed.
  - If you do not see “0” in the Dose Window you did not receive your full dose. Do not redial. Insert the needle into your skin and finish your injection.
  - If you still do not think you received the full amount you dialed for your injection, do not start over or repeat that injection. Monitor your blood sugar (glucose) and call your healthcare provider for further instructions.
  - If you normally need to give 2 injections for your full dose, be sure to give your second injection.
    The plunger only moves a little with each injection, and you may not notice that it moves.
    If you see blood after you take the Needle out of your skin, press the injection site lightly with a piece of gauze or an alcohol swab. Do not rub the area.

After your injection

Step 13:

- Carefully replace the Outer Needle Shield.

Step 14:

- Unscrew the capped Needle and throw it away (see Disposing of Pens and Needles section below).
- Do not store the Pen with the Needle attached to prevent leaking, blocking the Needle, and air from entering the Pen.

Step 15:

- Replace the Pen Cap by lining up the Cap Clip with the Dose Indicator and pushing straight on.

Disposing of Pens and Needles

- Put your used needles in a FDA-cleared sharps disposal container right away after use. Do not throw away (dispose of) loose needles in your household trash.
- If you do not have a FDA-cleared sharps disposal container, you may use a household container that is:
  - made of a heavy-duty plastic,
  - can be closed with a tight-fitting, puncture-resistant lid, without sharps being able to come out,
  - upright and stable during use,
  - leak-resistant, and
  - properly labeled to warn of hazardous waste inside the container.
- When your sharps disposal container is almost full, you will need to follow your community guidelines for the right way to dispose of your sharps disposal container. There may be state or local laws about how you should throw away used needles and syringes. For more information about safe sharps disposal, and for specific information about sharps disposal in the state that you live in, go to the FDA's website at: http://www.fda.gov/safesharpsdisposal
- Do not dispose of your used sharps disposal container in your household trash unless your community guidelines permit this. Do not recycle your used sharps disposal container.
- The used Pen may be thrown away (discarded) in your household trash after you have removed the needle.

Storing your BASAGLAR Tempo Pen

Unopened Pens

- Store unopened Pens in the refrigerator at 36°F to 46°F (2°C to 8°C).
- Do not freeze BASAGLAR. Do not use if it has been frozen.
- Unopened Pens may be used until the expiration date printed on the Label, if the Pen has been kept in the refrigerator.

In-use Pen

- Store the Pen you are currently using at room temperature [up to 86°F (30°C)] and away from heat and light.
- Throw away the Pen you are using after 28 days, even if it still has insulin left in it.

General information about the safe and effective use of your Pen

- Keep your Pen and needles out of the sight and reach of children.
- Always use a new needle for each injection.
- Do not share your Pen or needles with other people. You may give other people a serious infection or get a serious infection from them.
- Do not use your Pen if any part looks broken or damaged.
- Always carry an extra Pen in case yours is lost or damaged.

Troubleshooting

- If you cannot remove the Pen Cap, gently twist the cap back and forth, and then pull the cap straight off.
- If the Dose Knob is hard to push:
  - Pushing the Dose Knob more slowly will make it easier to inject.
  - Your Needle may be blocked. Put on a new Needle and prime the Pen.
  - You may have dust, food, or liquid inside the Pen. Throw the Pen away and get a new Pen.

If you have any questions or problems with your BASAGLAR Tempo Pen, contact Lilly at 1-800-LillyRx (1-800-545-5979) or call your healthcare provider for help. For more information on BASAGLAR Tempo Pen and insulin, go to www.basaglar.com.

Scan this code to launch

www.basaglar.com

This Instructions for Use have been approved by the U.S. Food and Drug Administration.

BASAGLAR® is a registered trademark and Tempo PenTM is a trademark of Eli Lilly and Company.

Instructions for Use revised: November 2022

Manufactured by:
Eli Lilly and Company
Indianapolis, IN 46285, USA
US License Number 1891

Copyright © 2021, 2022, Eli Lilly and Company. All rights reserved.

BASAGLAR Tempo Pen meets the current dose accuracy and functional requirements of ISO 11608-1.

BASTP-0004-IFU-20221115

PACKAGE CARTON – BASAGLAR KwikPen 80 UNIT PEN

Dispense in this sealed carton.

NDC 0002-7715-59

Basaglar®

KwikPen®

(insulin glargine)
injection

For Single Patient Use Only

100 units per mL (U-100)

For subcutaneous use only

Can inject from 1 to 80 units in a single injection

5 x 3 mL prefilled pens

prefilled insulin delivery device

Rx only

Read Basaglar® KwikPen® Instructions for Use.

NEEDLES NOT INCLUDED

This device is recommended for use with Becton, Dickinson & Company's insulin pen needles.

Lilly

PACKAGE CARTON – BASAGLAR Tempo Pen 80 UNIT PEN

Dispense in this sealed carton.

NDC 0002-8214-05

Basaglar®

Tempo Pen™

(insulin glargine)
injection

For Single Patient Use Only

100 units per mL (U-100)

For subcutaneous use only

Can inject from 1 to 80 units in a single injection

5 x 3 mL prefilled pens

prefilled insulin delivery device

Rx only

Read Basaglar® Tempo Pen™ Instructions for Use.

NEEDLES NOT INCLUDED

This device is recommended for use with Becton, Dickinson & Company's insulin pen needles.

Lilly